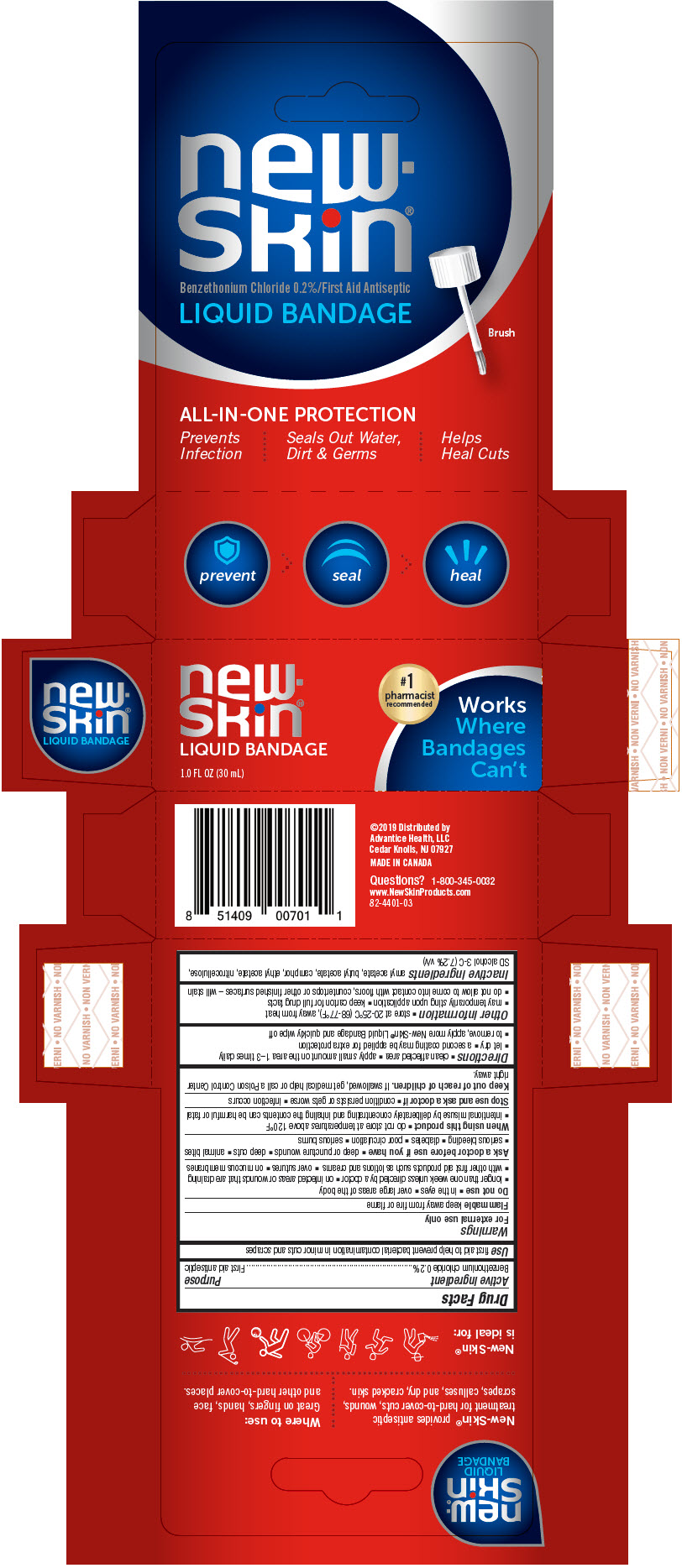 DRUG LABEL: New Skin Bandage
NDC: 16864-440 | Form: LIQUID
Manufacturer: Advantice Health, LLC
Category: otc | Type: HUMAN OTC DRUG LABEL
Date: 20260128

ACTIVE INGREDIENTS: BENZETHONIUM CHLORIDE 1.8 mg/1 mL
INACTIVE INGREDIENTS: ETHYL ACETATE; ACETONE; BUTYL ACETATE; AMYL ACETATE; ALCOHOL; PYROXYLIN; CAMPHOR (NATURAL)

New Skin Liquid Bandage

Drug Facts

Active ingredient

Benzethonium chloride 0.2%

Purpose

First aid antiseptic

Use

first aid to help prevent bacterial contamination in minor cuts and scrapes

Warnings

For external use only

Flammable

keep away from fire or flame

Do not use

- in the eyes
- over large areas of the body
- longer than one week unless directed by a doctor
- on infected areas or wounds that are draining
- with other first aid products such as lotions and creams
- over sutures
- on mucous membranes

Ask a doctor before use if you have

- deep or puncture wounds
- deep cuts
- animal bites
- serious bleeding
- diabetes
- poor circulation
- serious burns

When using this product

- do not store at temperatures above 120°F
- intentional misuse by deliberately concentrating and inhaling the contents can be harmful or fatal

Stop use and ask a doctor if

- condition persists or gets worse
- infection occurs

Keep out of reach of children.If swallowed, get medical help or call a Poison Control Center right away.

Directions

- clean affected area
- apply small amount on the area 1–3 times daily
- let dry
- a second coating may be applied for extra protection
- to remove, apply more New-Skin®Liquid Bandage and quickly wipe off

Other information

- store at 20-25°C (68-77°F), away from heat
- may temporarily sting upon application
- keep carton for full drug facts
- do not allow to come into contact with floors, countertops or other finished surfaces – will stain

Inactive ingredients

amyl acetate, butyl acetate, camphor, ethyl acetate, nitrocellulose, SD alcohol 3-C (7.2% v/v)

Questions?

1-800-345-0032

Distributed by
Advantice Health, LLC
Cedar Knolls, NJ 07927

PRINCIPAL DISPLAY PANEL - 30 mL Bottle Box

new-
Skin®

Benzethonium Chloride 0.2%/First Aid Antiseptic

LIQUID BANDAGE

Brush

ALL-IN-ONE PROTECTION

Prevents
Infection

Seals Out Water,
Dirt & Germs

Helps
Heal Cuts

#1
pharmacist
recommended

Works
Where
Bandages
Can't

1.0 FL OZ (30 mL)